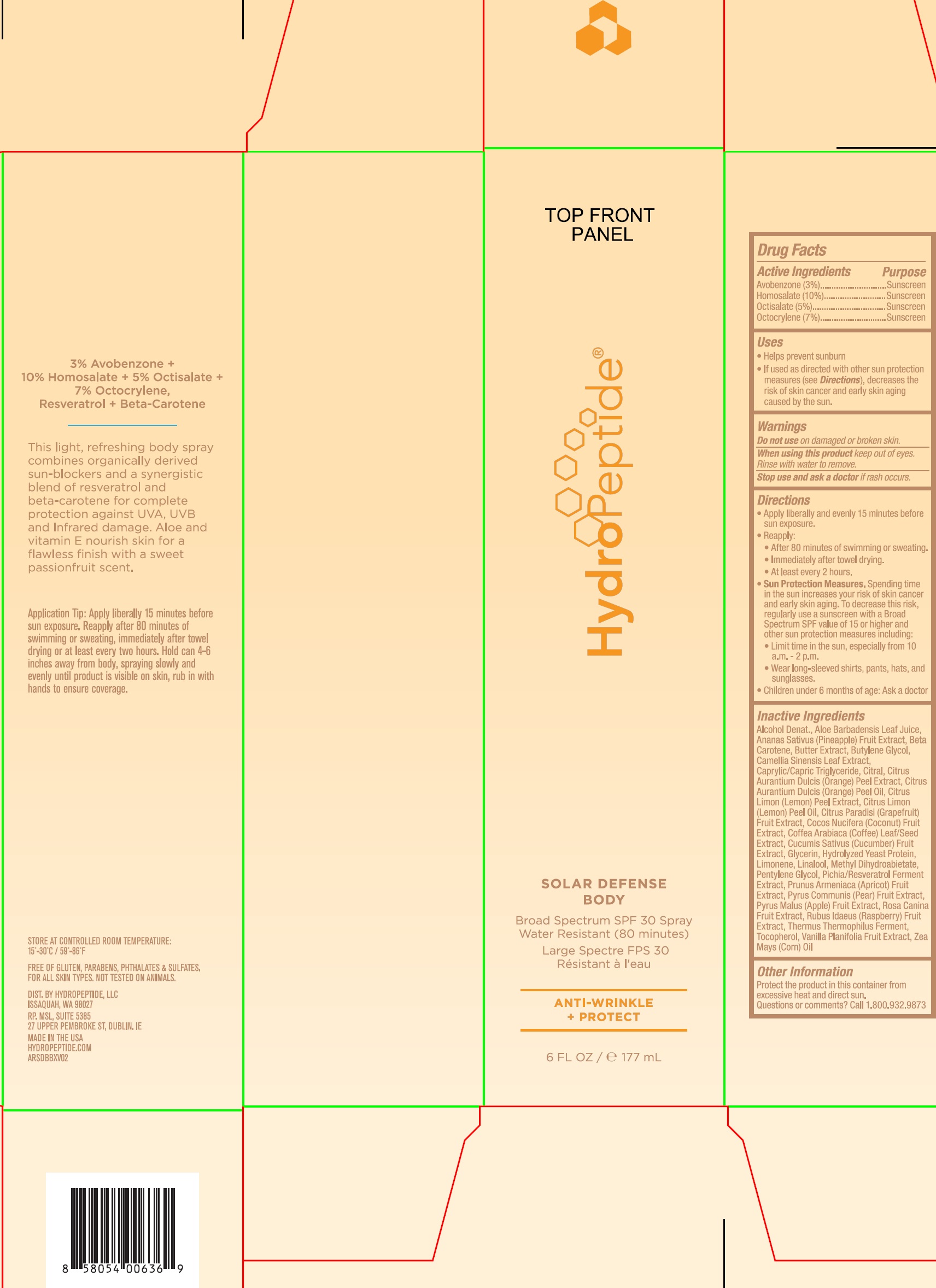 DRUG LABEL: Solar Defense Body
NDC: 60934-004 | Form: AEROSOL, SPRAY
Manufacturer: HydroPeptide LLC
Category: otc | Type: HUMAN OTC DRUG LABEL
Date: 20231209

ACTIVE INGREDIENTS: AVOBENZONE 30 mg/1 mL; HOMOSALATE 100 mg/1 mL; OCTISALATE 50 mg/1 mL; OCTOCRYLENE 70 mg/1 mL
INACTIVE INGREDIENTS: ALCOHOL; PINEAPPLE; BETA CAROTENE; BUTYLENE GLYCOL; GREEN TEA LEAF; MEDIUM-CHAIN TRIGLYCERIDES; CITRAL; ORANGE PEEL; LEMON OIL; GRAPEFRUIT; COCONUT; COFFEE BEAN; CUCUMBER; GLYCERIN; LIMONENE, (+)-; LINALOOL, (+/-)-; METHYL DIHYDROABIETATE; PENTYLENE GLYCOL; APRICOT; PEAR; APPLE; ROSA CANINA FRUIT; RASPBERRY; THERMUS THERMOPHILUS LYSATE; TOCOPHEROL; VANILLA; CORN

Solar Defense Body

Active Ingredients

Avobenzone (3%)

Homosalate (10%)

Octisalate (5%)

Octocrylene (7%)

Purpose

Sunscreen

Uses

- Helps prevent sunburn
- If used as directed with other sun protection measures (see), decreases the risk of skin cancer and early skin aging caused by the sun. Directions

Warnings

Do not use

on damaged or broken skin.

When using this product

keep out of eyes. Rinse with water to remove.

Stop use and ask a doctor

if rash occurs.

Keep out of reach of children.

If product is swallowed, get medical help or contact a Poison Control Center right away.

Directions

- Apply liberally and evenly 15 minutes before sun exposure.
- Reapply:
- After 80 minutes of swimming or sweating.
- Immediately after towel drying.
- At least every 2 hours.
- Sun Protection Measures. Spending time in the sun increases your risk of skin cancer and early skin aging. To decrease this risk, regularly use a sunscreen with a Broad Spectrum SPF value of 15 or higher and other sun protection measures including:
- Limit itme in the sun, expecially from 10 a.m. - 2 p.m.
- Wear long-sleeved shirts, pants, hats, and sunglasses.
- Children under 6 months of age: Ask a Doctor

Inactive Ingredients

Alcohol Denat., Aloe Barbadensis Leaf Juice, Ananas Sativus (Pineapple) Fruit Extract, Beta Carotene, Butter Extract, Butylene Glycol, Camellia Sinensis Leaf Extract, Caprylic/Capric Triglyceride, Citral, Citrus Aurantium Dulcis (Orange) Peel Extract, Citrus Aurantium Dulcis (Orange) Peel Oil, Citrus Limon (Lemon) Peel Oil, Citrus Paradisi (Grapefruit) Fruit Extract, Cocos Nucifera (Coconut) Fruit Extract, Coffea Arabiaca (Coffee) Leaf/ Seed Extract, Cucumis Sativus (Cucumber) Fruit Extract, Glycerin, Hydrolyzed Yeast Protein, Limonene, Linalool, Methyl Dihydroabietate, Pentylene Glycol, Pichia/Resveratrol Ferment Extract, Prunus Armeniaca (Apricot) Fruit Extract, Pyrus Communis (Pear) Fruit Extract, Pyrus Malus (Apple) Fruit Extract, Rosa Canina Fruit Extract, Rubus Idaeus (Raspberry) Fruit Extract, Thermus Thermophilus Ferment, Tocopherol, Vanilla Planifolia Fruit Extract, Zea Mays (Corn) Oil

Other Information

Protect the product in this container from excessive heat and direct sun.

Questions or comments?

Call 1.800.932.9873